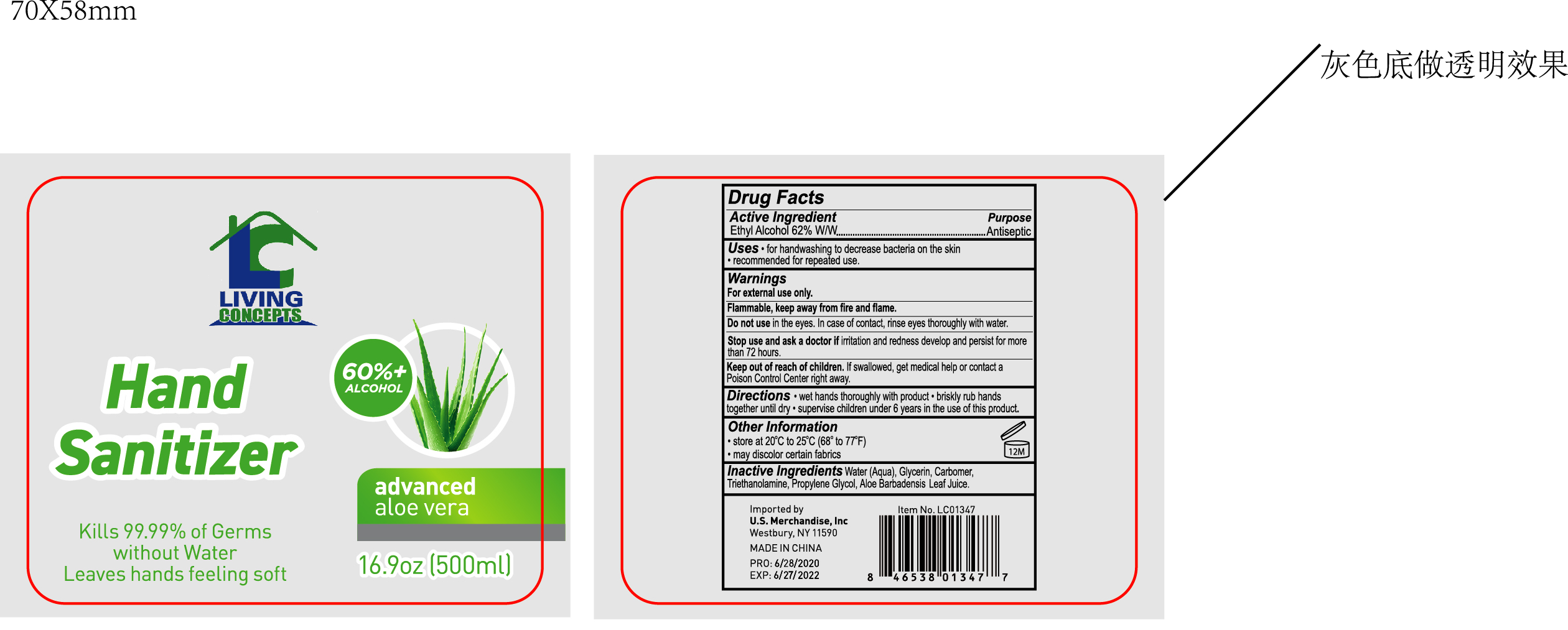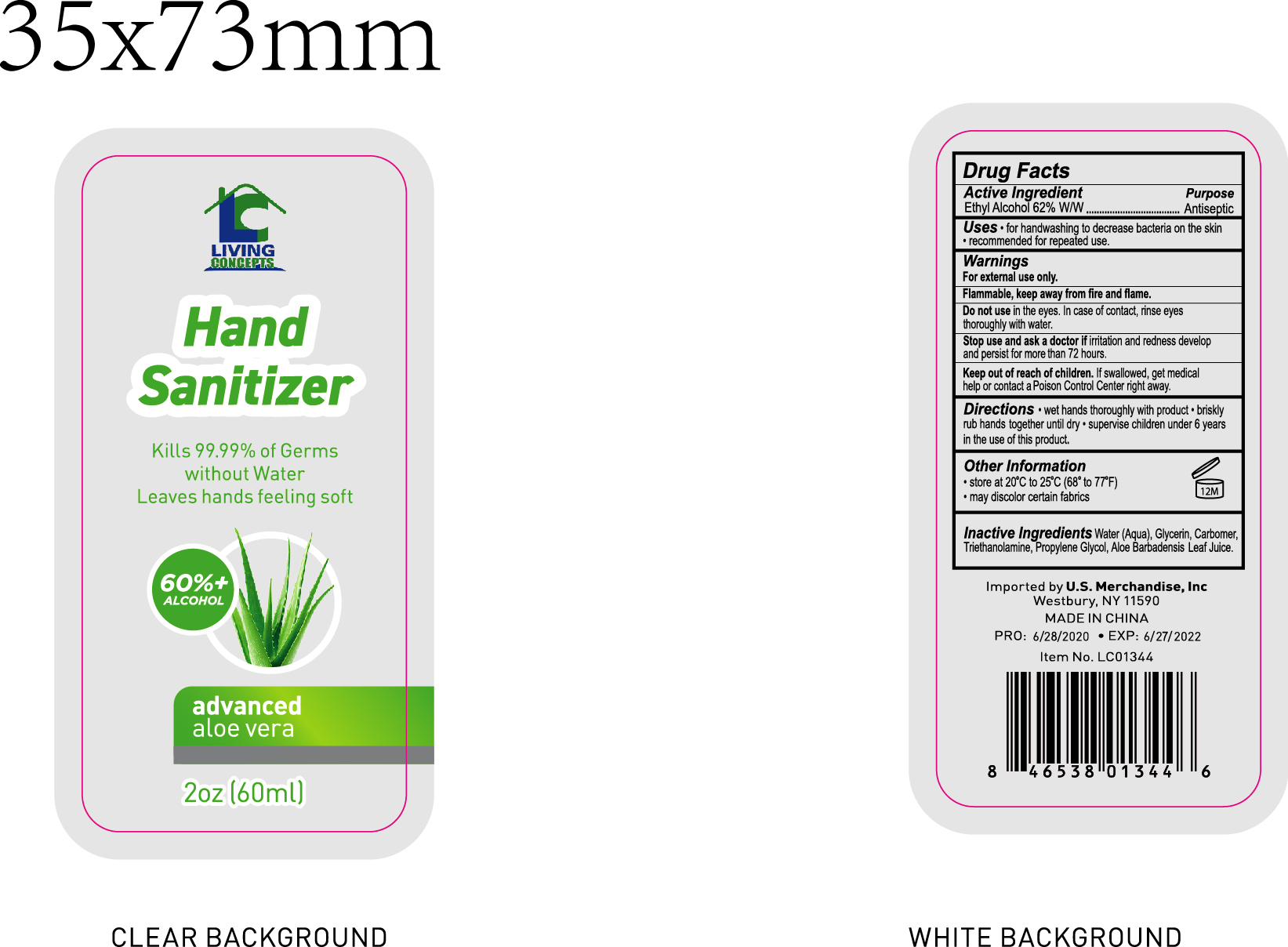 DRUG LABEL: HAND SANITIZER
NDC: 76681-001 | Form: GEL
Manufacturer: Taizhou Huangyan Delishi Daily Necessity Co., Ltd.
Category: otc | Type: HUMAN OTC DRUG LABEL
Date: 20200630

ACTIVE INGREDIENTS: ALCOHOL 62 mL/100 mL
INACTIVE INGREDIENTS: GLYCERIN; TROLAMINE; WATER; PROPYLENE GLYCOL; ALOE VERA LEAF; CARBOMER 934

HAND SANITIZER

Purpose

Antiseptic

Use

. for handwashing to decrease bacteria on the skin

Warnings

For external use only. Flammable. Keep away from hear and flame.

Do not use. In the eyes. In case of contact, rinse eyes thoroughly with water.

WHEN USING

/

Stop use and ask a doctor if irritation or redness develops and persists for more than 72 hours.

Keep out of reach of children. If swallowed, get medical help or contact a Poison Control Center right away.

Directions

Wet hands thoroughly with product . briskly rub hands together until dry.

Supervise children under 6 years in theuse of this product.

Other information

Store at 20℃ to 25℃ [68°-77°F]

May discolor certain fabrics

Inactive ingredients

Water (Aqua), Glycerin, Carbomer, Triethanolamine, Propylene Glycol, Aloe Barbadensis Leaf Juice.

ACTIVE INGREDIENT

Ethyl Alcohol 62% v/v